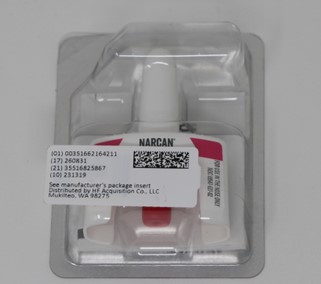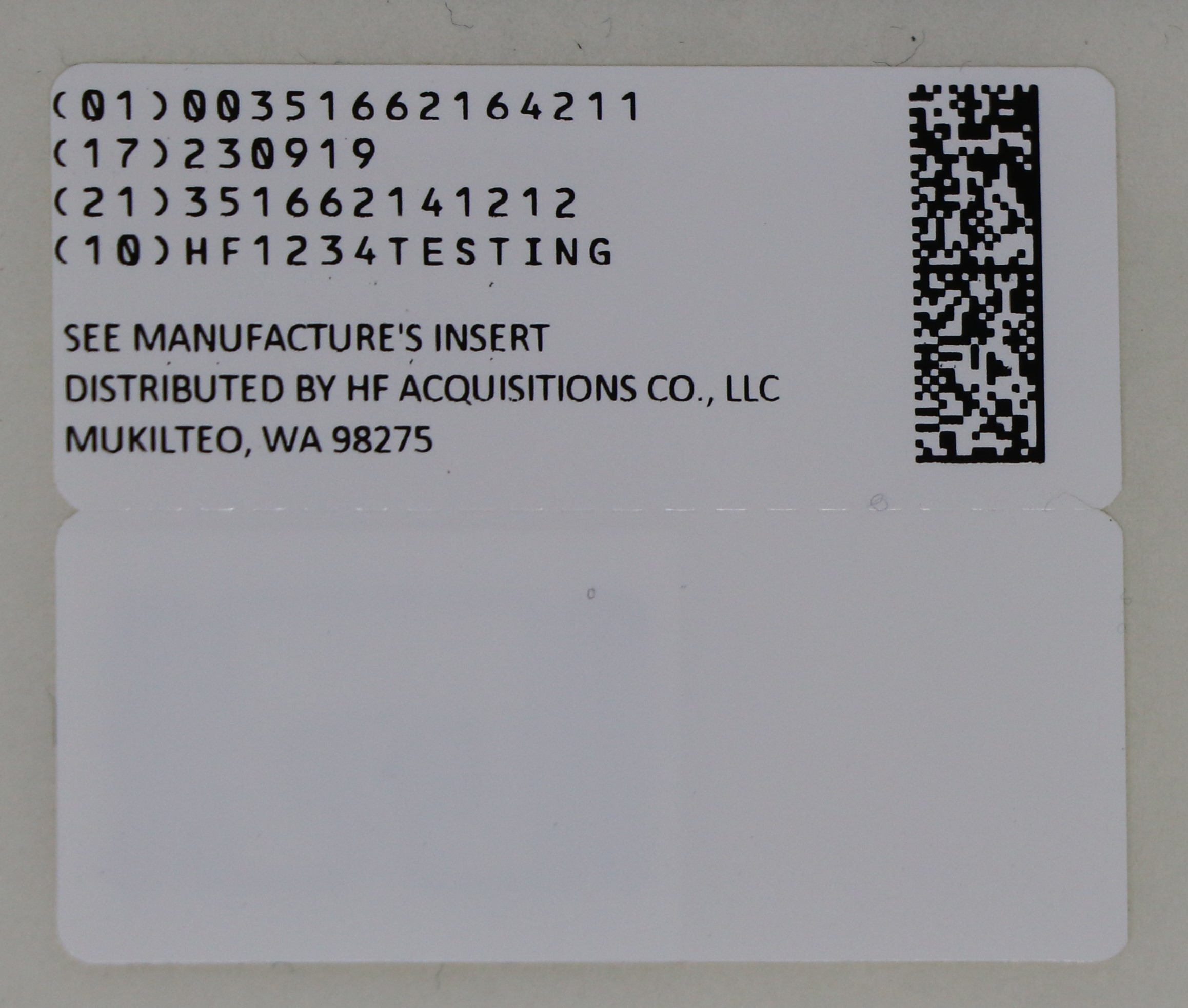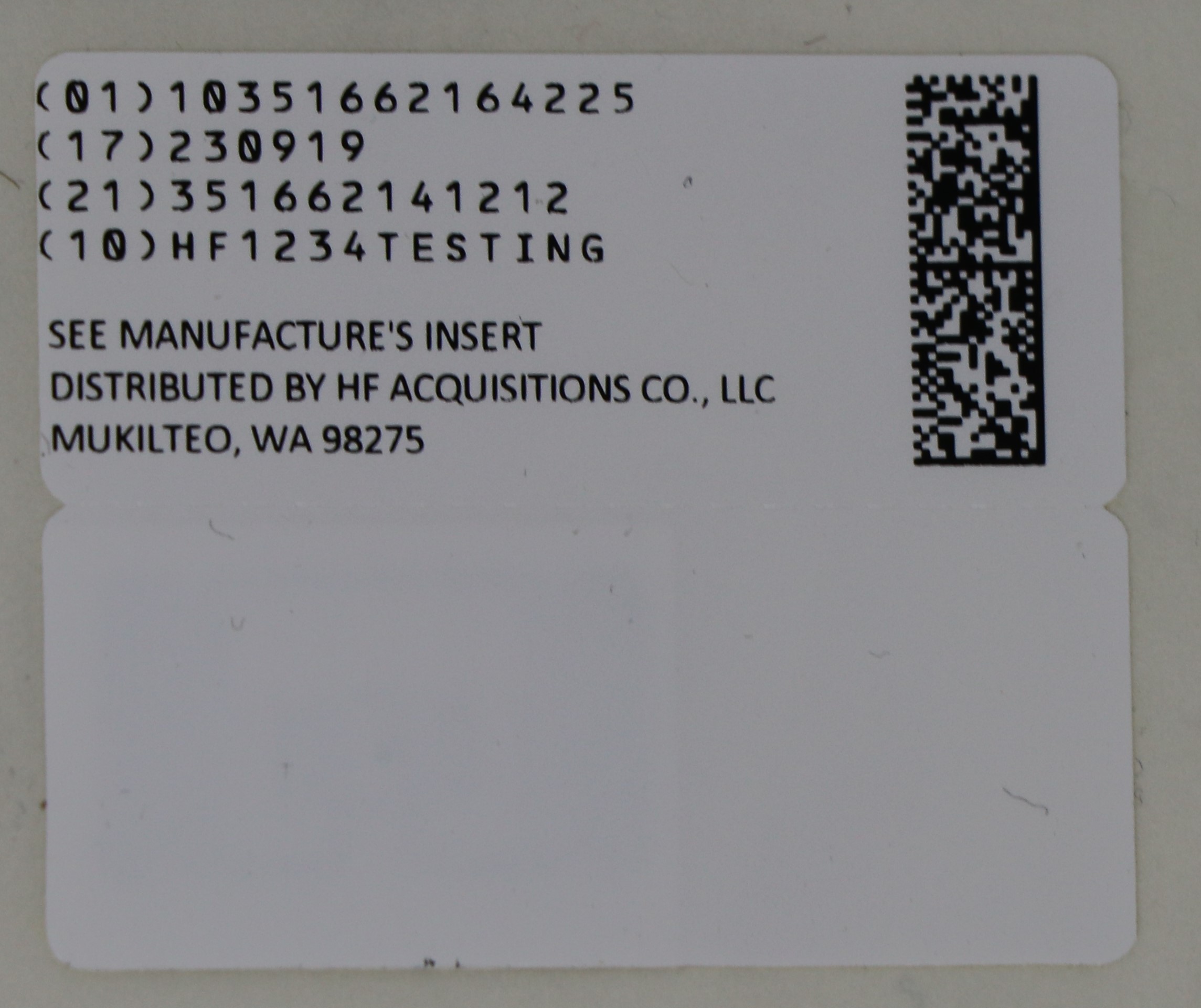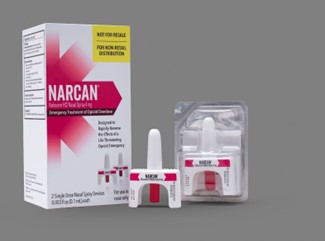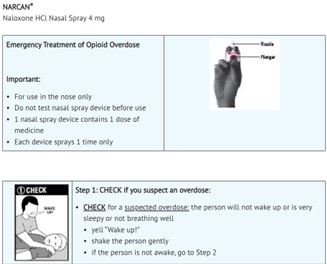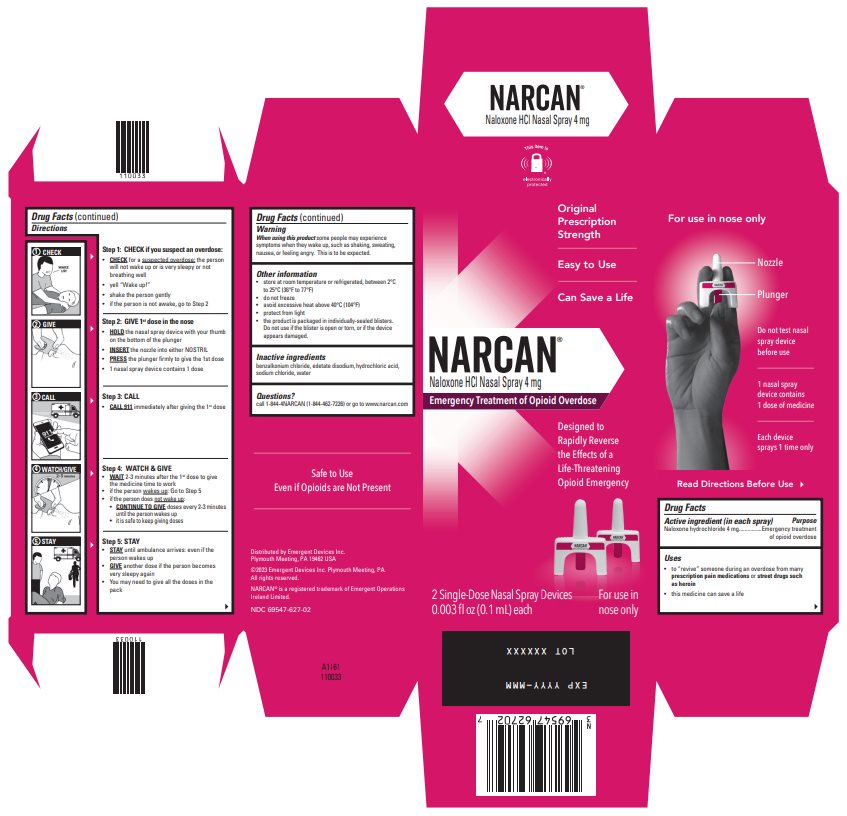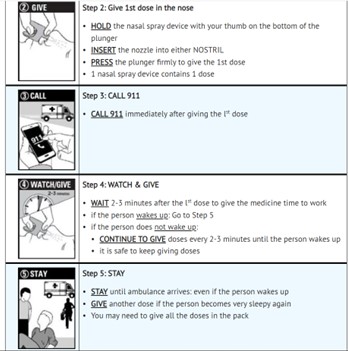 DRUG LABEL: Narcan Naloxone HCL
NDC: 51662-1642 | Form: SPRAY
Manufacturer: HF Acquisition Co LLC, DBA HealthFirst
Category: otc | Type: HUMAN OTC DRUG LABEL
Date: 20240220

ACTIVE INGREDIENTS: NALOXONE HYDROCHLORIDE 4 mg/0.1 mL
INACTIVE INGREDIENTS: HYDROCHLORIC ACID; EDETATE DISODIUM; SODIUM CHLORIDE; BENZALKONIUM CHLORIDE; WATER

ACTIVE INGREDIENT (IN EACH SPRAY)

Naloxone Hydrochloride 4 mg

PURPOSE

Emergency treatment of opioid overdose

USES

- to “revive” someone during an overdose from many prescription pain medications or street drugs such as heroin
- this medicine can save a life

When using this product some people may experience symptoms when they wake up, such as, shaking, sweating, nausea, or feeling angry. This is to be expected.

DIRECTIONS

For opioid emergencies, call 911. For questions on NARCAN, call 1-844-4NARCAN (1-844-462-7226) or go to WWW.NARCAN.COM.

©2023 Emergent Devices Inc. EMERGENT® and NARCAN® are registered trademarks of Emergent BioSolutions Inc, or its subsidiaries.

Other Information

•
store at room temperature or refrigerated, between 2°C to 25°C (36°F to 77°F)
•
do not freeze
•
avoid excessive heat above 40°C (104°F)
•
protect from light
•
the product is packaged in individually-sealed blisters.

Do not use if the blister is open or torn, or if the device appears damaged.

INACTIVE INGREDIENT

benzalkonium chloride, edetate disodium, hydrochloric acid, sodium chloride, water

QUESTIONS

Call 1-844-4NARCAN (1-844-462-7226) or go to WWW.NARCAN.COM

keep out of reach of children